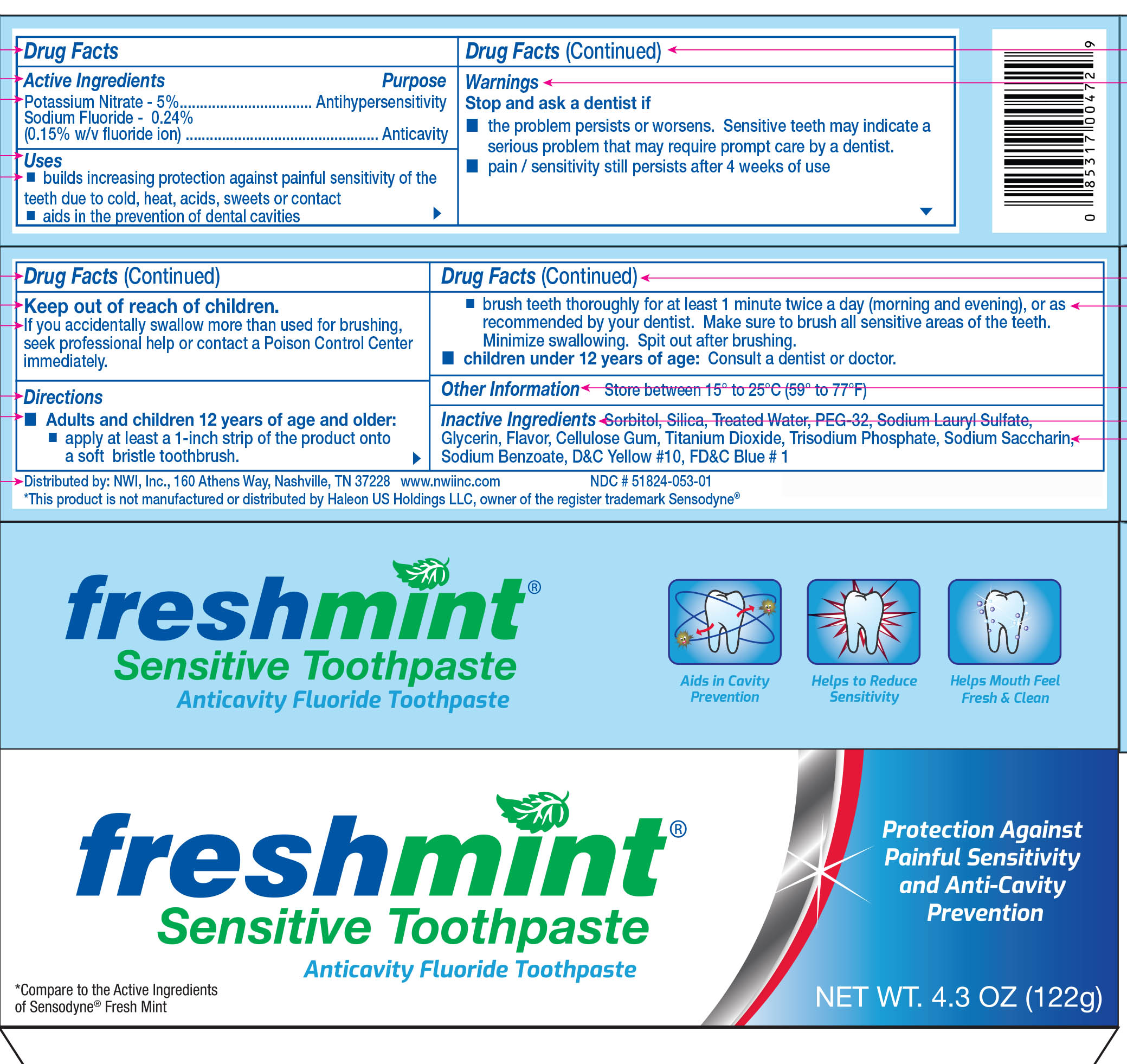 DRUG LABEL: Freshmint Sensitive
NDC: 51824-053 | Form: PASTE, DENTIFRICE
Manufacturer: New World Imports, Inc
Category: otc | Type: HUMAN OTC DRUG LABEL
Date: 20251201

ACTIVE INGREDIENTS: SODIUM FLUORIDE 2.4 mg/1 g; POTASSIUM NITRATE 50 mg/1 g
INACTIVE INGREDIENTS: SORBITOL; SILICON DIOXIDE; WATER; POLYETHYLENE GLYCOL 1600; SODIUM LAURYL SULFATE; GLYCERIN; CARBOXYMETHYLCELLULOSE SODIUM, UNSPECIFIED; TITANIUM DIOXIDE; SODIUM PHOSPHATE, TRIBASIC, DODECAHYDRATE; SACCHARIN SODIUM; SODIUM BENZOATE; D&C YELLOW NO. 10; FD&C BLUE NO. 1

Drug Facts

Active Ingredients

Potassium Nitrate - 5%

Sodium Fluoride - 0.24%

Purpose

Potassium Nitrate - Antihypersensitivity

Sodium Fluoride - Anticavity

Keep out of reach of Children

If you accidentally swallow more than used for brushing, seek professional help or contact a Poison Control Center immediately.

Uses

Builds increasing protection against painful sensitivity of teeth due to cold, heat, acids, sweets or contact.

Aids in the prevention of dental cavities

Warnings

Stop and ask a dentistif

- The problem persists or worsens. Sensitive teeth may indicate a serious problem that may require prompt care by a dentist
- Pain / sensitivity still persists after 4 weeks of use

Directions

Adults and children 12 years and older:

- Apply at least a 1-inch strip of the product onto a soft bristle toothbrush.
- Brush teet thoroughly for at least 1 minute twice a day (morning and evening), or as recommended by your dentist. Make sure to brush all sensitive areas of the teeth. Minimize swallowing. Spit out after brushing

Children under 12 years of age:consult a doctor.

Inactive Ingredients

Sorbitol, Silica, Treated Water, PEG-32, Sodium Lauryl Sulfate, Glycerin, Flavor, Cellulose Gum, Titanium Dioxide, Trisodium Phosphate, Sodium Saccharin, Sodium Benzoate, Color: D and C Yellow # 10, FD and C Blue # 1.